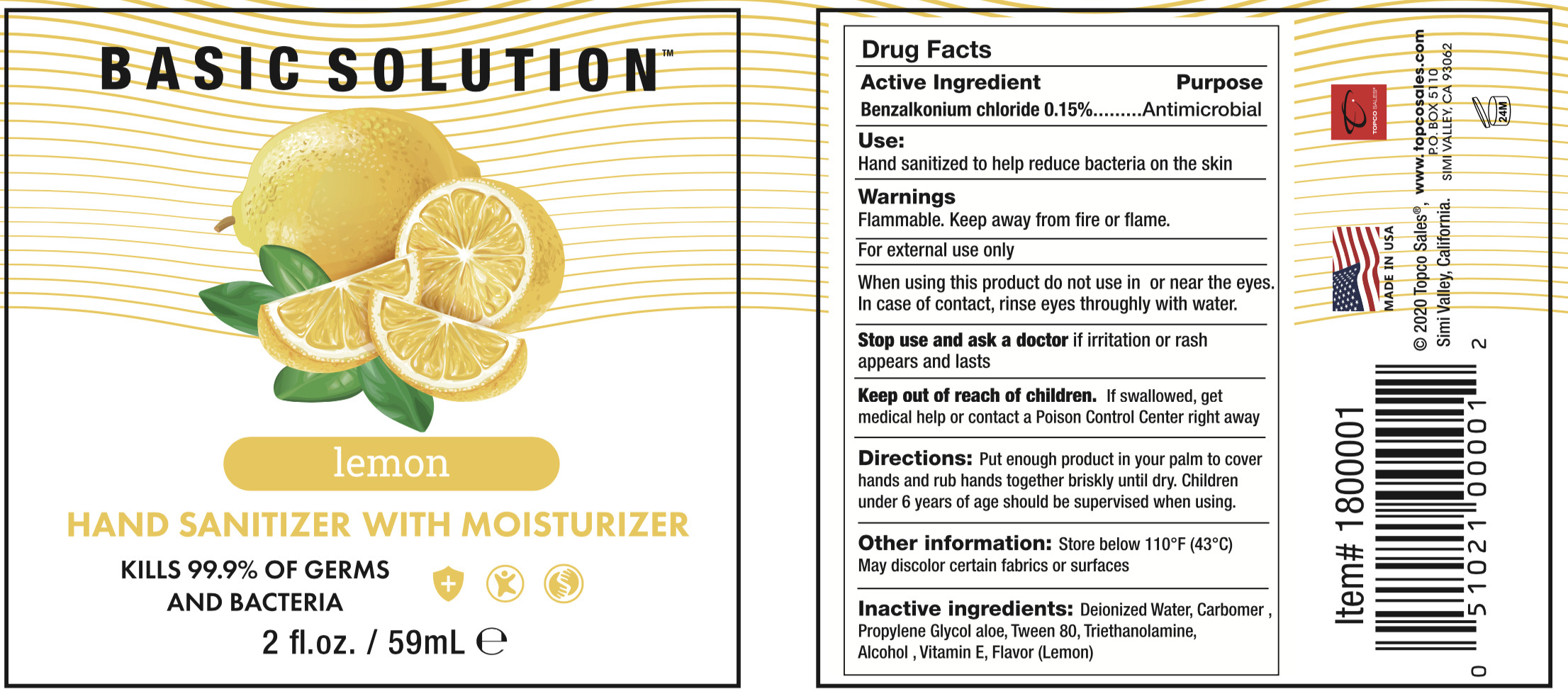 DRUG LABEL: Basic Solutions Hand sanitizer with moisturizer 2 OZ lemon
NDC: 69797-002 | Form: GEL
Manufacturer: Wsm Investments, LLC Topco Sales
Category: otc | Type: HUMAN OTC DRUG LABEL
Date: 20200610

ACTIVE INGREDIENTS: ALCOHOL 41.3 mL/59 mL
INACTIVE INGREDIENTS: PROPYLENE GLYCOL; ALOE; CARBOMER HOMOPOLYMER, UNSPECIFIED TYPE; TROLAMINE; BENZALKONIUM CHLORIDE; POLYSORBATE 80; WATER; LEMON

DOSAGE AND ADMINISTRATION

Store below 110°F (43°C)

INACTIVE INGREDIENT

Deionized Water、Propylene Glycol、Aloe、Tween 80、Carbomer、Triethanolamine、Benzalkonium chloride、Scan（Lemon）

INDICATIONS AND USAGE

Put enough product in your palm to cover hands and ub hands together briskly until dry.

ACTIVE INGREDIENT

Ethyl alcohol

keep out of reach of children

PURPOSE

Disinfection
Sterilization
No Rinseing

WARNINGS

Flammable. Keep away from fire or flame.